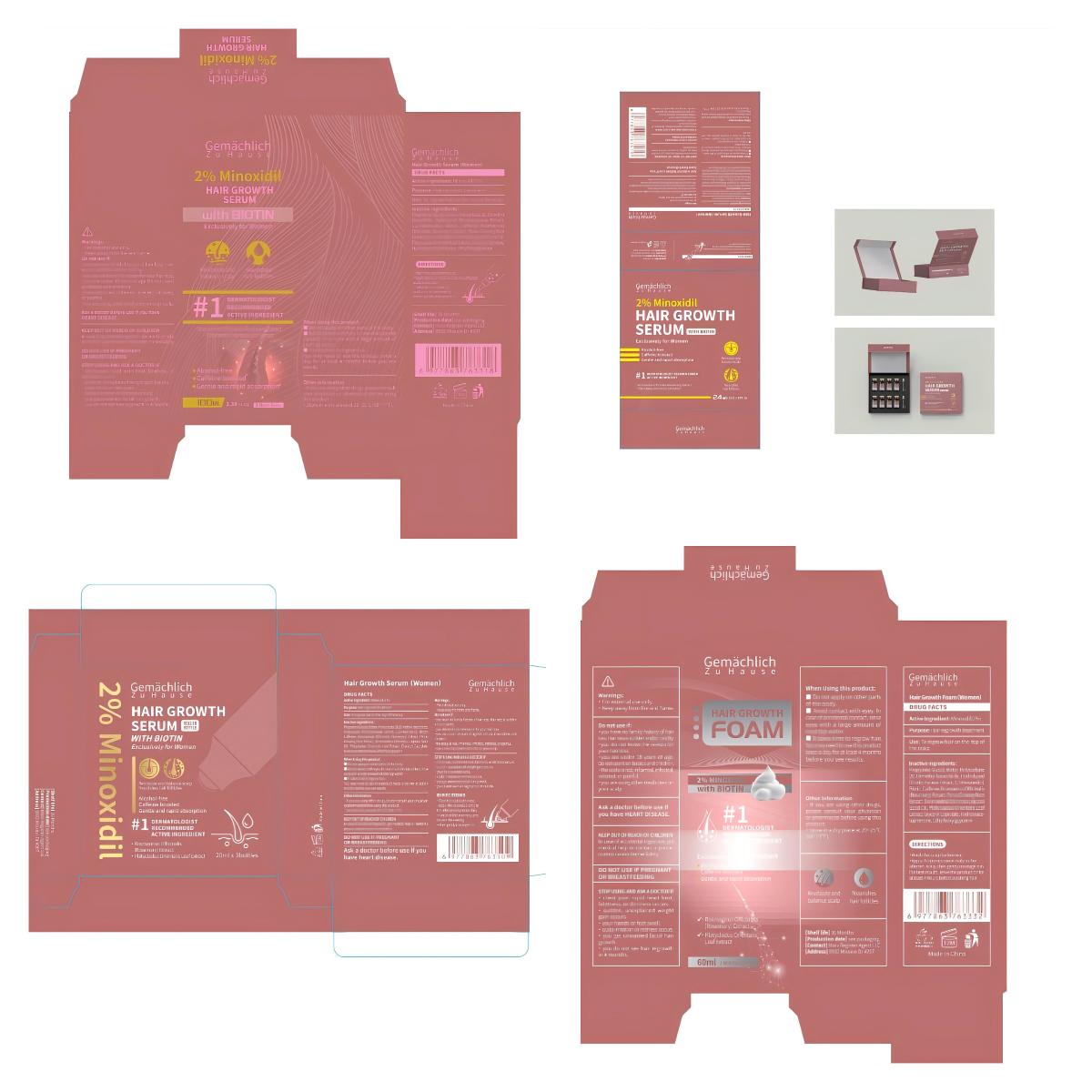 DRUG LABEL: Gemachlich ZuHause Hair Growth Serum (Women)
NDC: 76986-012 | Form: LIQUID
Manufacturer: Guangdong Quadrant Ecological Technology Co., Ltd.
Category: otc | Type: HUMAN OTC DRUG LABEL
Date: 20250904

ACTIVE INGREDIENTS: MINOXIDIL 2 g/100 mL
INACTIVE INGREDIENTS: CAFFEINE; DIMETHYL ISOSORBIDE; PANAX GINSENG ROOT; GLYCERYL CAPRYLATE; POLYSORBATE 20; BIOTIN; WATER; ETHYLHEXYLGLYCERIN; 1,2-HEXANEDIOL; ROSMARINUS OFFICINALIS (ROSEMARY) LEAF POWDER; HABERLEA RHODOPENSIS WHOLE; SIMMONDSIA CHINENSIS (JOJOBA) SEED OIL; PROPYLENE GLYCOL; HYDROXYACETOPHENONE

76986-012

Active Ingredient

Minoxidil 2%

Purpose

Hair regrowth treatment

Use

To regrow hair on the top of the scalp .

Warnings

· For external use only.
· Keep away from fire and flame.

Do not use if
·you have no family history of hair loss. Hair loss is sudden and/or patchy.
·you do not know the reason for your hair loss.
·you are under 18 years of age.Do not use it on babies and children.
·the scalp is red, inflamed, infected, irritated, or painful.
·you are using other medicines on your scalp.

When Using

When Using this product:
■ Do not apply on other parts of the body.
■ Avoid contact with eyes. In case of accidental contact, rinse eyes with a large amount of cool tap water.
■ lt takes time to regrow hair.
You may need to use this product twice a day for at least 4 months before you see results.

Stop Use

Stop Using and ask a doctor if
· chest pain, rapid heart beat, faintness, or dizziness occurs.
· sudden, unexplained weight gain occurs.
· your hands or feet swell.
· scalp irritation or redness occurs.
· you get unwanted facial hair growth.
· you do not see hair regrowth in 4 months.

Ask Doctor

Stop Using and ask a doctor if
· chest pain, rapid heart beat, faintness, or dizziness occurs.
· sudden, unexplained weight gain occurs.
· your hands or feet swell.
· scalp irritation or redness occurs.
· you get unwanted facial hair growth.
· you do not see hair regrowth in 4 months.

Keep out of reach of Children. In case of accidental ingestion, get medical help or contact a poison control center immediately.

Directions

.Wash the scalp before use .
.Apply the serum(0.5ml-1ml) to the affected scalp twice daily—once in the morning and once in the evening—then gently massage it in.

Other information

· If you are using other drugs, please consult your physician or pharmacist before using this product.
· Store in a dry place at 20~25°C (68~77°F).

Inactive ingredients

Propylene Glycol, Water, Polysorbate 20, Dimethyl Isosorbide, Hydrolyzed Rhodophyceae Extract, 1,2-Hexanediol, Biotin, Caffeine, Rosmarinus Officinalis (Rosemary) Extract, Panax Ginseng Root Extract, Simmondsia Chinensis (Jojoba) Seed Oil, Platycladus Orientalis Leaf Extract, Glyceryl Caprylate, Hydroxyacetophenone, Ethylhexylglycerin